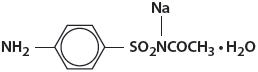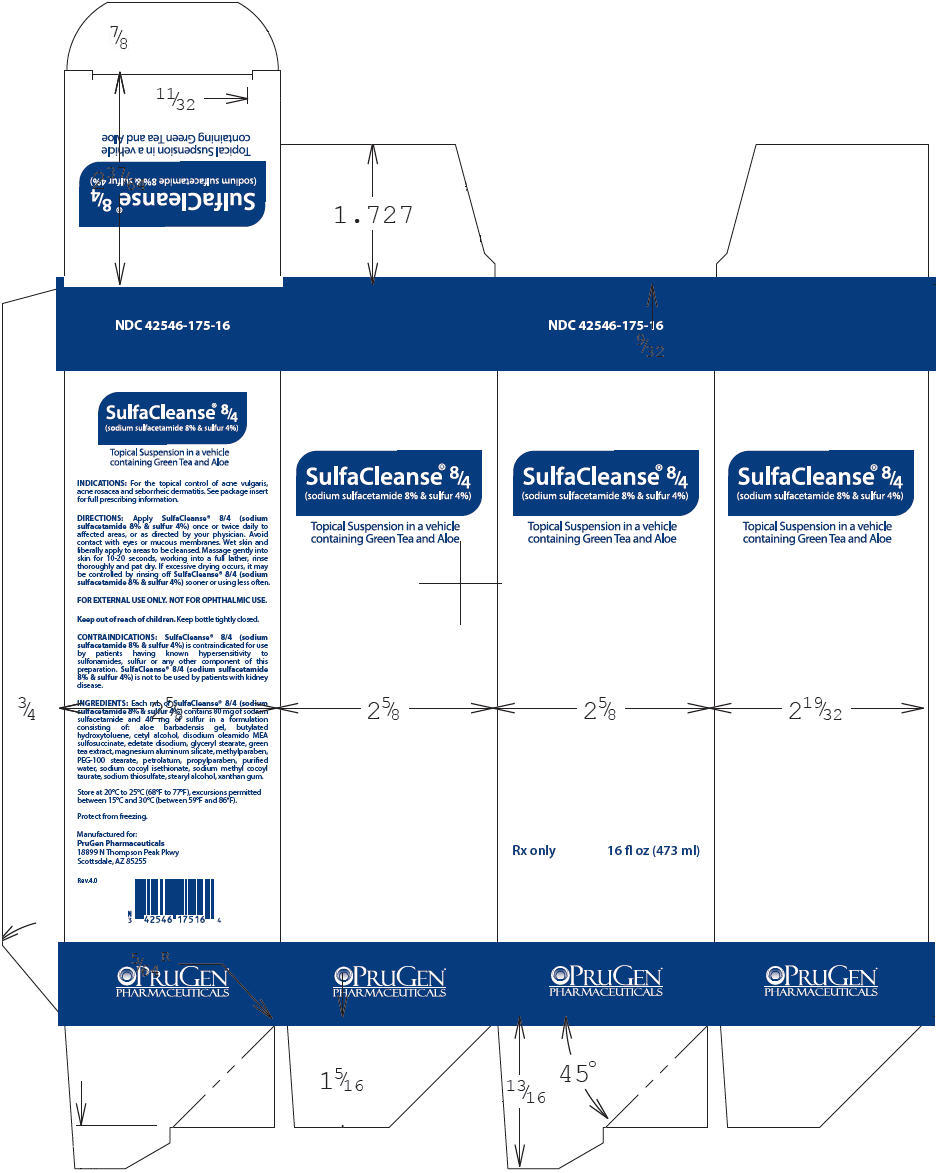 DRUG LABEL: SulfaCleanse 8/4
NDC: 42546-175 | Form: LOTION
Manufacturer: PruGen, Inc.
Category: prescription | Type: HUMAN PRESCRIPTION DRUG LABEL
Date: 20220120

ACTIVE INGREDIENTS: SULFACETAMIDE SODIUM 80 mg/1 mL; SULFUR 40 mg/1 mL
INACTIVE INGREDIENTS: Aloe; BUTYLATED HYDROXYTOLUENE; Cetyl alcohol; DISODIUM OLEAMIDO MONOETHANOLAMINE SULFOSUCCINATE; EDETATE DISODIUM; GLYCERYL MONOSTEARATE; Green tea leaf; MAGNESIUM ALUMINUM SILICATE; METHYLPARABEN; PEG-100 STEARATE; PROPYLPARABEN; WATER; SODIUM COCOYL ISETHIONATE; TAURINE; SODIUM THIOSULFATE; STEARYL ALCOHOL; XANTHAN GUM

SulfaCleanse® ^8/4
(sodium sulfacetamide 8% & sulfur 4%)

Rx Only

Topical Suspension in a vehicle containing Green Tea and Aloe

DESCRIPTION

Sodium sulfacetamide is a sulfonamide with antibacterial activity while sulfur acts as a keratolytic agent. Chemically sodium sulfacetamide is N-[(4-aminophenyl) sulfonyl]-acetamide, monosodium salt, monohydrate. The structural formula is:

Each mL of SulfaCleanse® 8/4 (sodium sulfacetamide 8% & sulfur 4%) contains 80 mg of sodium sulfacetamide and 40 mg of sulfur in a formulation consisting of: aloe barbadensis gel, butylated hydroxytoluene, cetyl alcohol, disodium oleamido MEA sulfosuccinate, edetate disodium, glyceryl stearate, green tea extract, magnesium aluminum silicate, methylparaben, PEG-100 stearate, petrolatum, propylparaben, purified water, sodium cocoyl isethionate, sodium methyl cocoyl taurate, sodium thiosulfate, stearyl alcohol, xanthan gum.

CLINICAL PHARMACOLOGY

The most widely accepted mechanism of action of sulfonamides is the Woods-Fildes theory, which is based on the fact that sulfonamides act as competitive antagonists to paraaminobenzoic acid (PABA), an essential component for bacterial growth. While absorption through intact skin has not been determined, sodium sulfacetamide is readily absorbed from the gastrointestinal tract when taken orally and excreted in the urine, largely unchanged. The biological half-life has variously been reported as 7 to 12.8 hours. The exact mode of action of sulfur in the treatment of acne is unknown, but it has been reported that it inhibits the growth of Propionibacterium acnes and the formation of free fatty acids.

INDICATIONS

SulfaCleanse® 8/4 (sodium sulfacetamide 8% & sulfur 4%) is indicated for the topical control of acne vulgaris, acne rosacea and seborrheic dermatitis.

CONTRAINDICATIONS

SulfaCleanse® 8/4 (sodium sulfacetamide 8% & sulfur 4%) is contraindicated for use by patients having known hypersensitivity to sulfonamides, sulfur or any other component of this preparation. SulfaCleanse® 8/4 (sodium sulfacetamide 8% & sulfur 4%) is not to be used by patients with kidney disease.

WARNINGS

Although rare, sensitivity to sodium sulfacetamide may occur. Therefore, caution and careful supervision should be observed when prescribing this drug for patients who may be prone to hypersensitivity to topical sulfonamides. Systemic toxic reactions such as agranulocytosis, acute hemolytic anemia, purpura hemorrhagica, drug fever, jaundice, and contact dermatitis indicate hypersensitivity to sulfonamides. Particular caution should be employed if areas of denuded or abraded skin are involved.

FOR EXTERNAL USE ONLY. Keep away from eyes. Keep out of reach of children. Keep container tightly closed.

PRECAUTIONS

General

If irritation develops, use of the product should be discontinued and appropriate therapy instituted. Patients should be carefully observed for possible local irritation or sensitization during long-term therapy. The object of this therapy is to achieve desquamation without irritation, but sodium sulfacetamide and sulfur can cause reddening and scaling of the epidermis. These side effects are not unusual in the treatment of acne vulgaris, but patients should be cautioned about the possibility.

Information for Patients

Avoid contact with eyes, eyelids, lips and mucous membranes. If accidental contact occurs, rinse with water. If excessive irritation develops, discontinue use and consult your physician.

Carcinogenesis, Mutagenesis and Impairment of Fertility

Long-term studies in animals have not been performed to evaluate carcinogenic potential.

PREGNANCY

Category C

Animal reproduction studies have not been conducted with SulfaCleanse® 8/4 (sodium sulfacetamide 8% & sulfur 4%). It is also not known whether SulfaCleanse® 8/4 (sodium sulfacetamide 8% & sulfur 4%) can cause fetal harm when administered to a pregnant woman or can affect reproduction capacity. SulfaCleanse® 8/4 (sodium sulfacetamide 8% & sulfur 4%) should be given to a pregnant woman only if clearly needed.

NURSING MOTHERS

It is not known whether sodium sulfacetamide is excreted in the human milk following topical use of SulfaCleanse® 8/4 (sodium sulfacetamide 8% & sulfur 4%). However, small amounts of orally administered sulfonamides have been reported to be eliminated in human milk. In view of this and because many drugs are excreted in human milk, caution should be exercised when SulfaCleanse® 8/4 (sodium sulfacetamide 8% & sulfur 4%) is administered to a nursing woman.

PEDIATRIC USE

Safety and effectiveness in children under the age of 12 has not been established.

ADVERSE REACTIONS

Although rare, sodium sulfacetamide may cause local irritation.

DOSAGE AND ADMINISTRATION

Apply SulfaCleanse® 8/4 (sodium sulfacetamide 8% & sulfur 4%) once or twice daily to affected areas, or as directed by your physician. Wet skin and liberally apply to areas to be cleansed. Massage gently into skin for 10-20 seconds, working into a full lather, rinse thoroughly and pat dry. If drying occurs, it may be controlled by rinsing off SulfaCleanse® 8/4 (sodium sulfacetamide 8% & sulfur 4%) sooner or using less often.

HOW SUPPLIED

SulfaCleanse® 8/4 (sodium sulfacetamide 8% & sulfur 4%) is available in a 16 fl. oz. (473 mL) bottle, NDC 42546-175-16.

STORAGE AND HANDLING

Store at 20°C to 25°C (68°F to 77°F), excursions permitted between 15°C and 30°C (between 59°F and 86°F). Brief exposure to temperatures up to 40°C (104°F) may be tolerated provided the mean kinetic temperature does not exceed 25°C (77°F); however, such exposure should be minimized.

Protect from freezing.

KEEP THIS AND ALL MEDICATIONS OUT OF THE REACH OF CHILDREN.

Manufactured for:
PruGen Pharmaceuticals
18899 N Thompson Peak Pkwy
Scottsdale, AZ 85255

Rev.4.0

PRINCIPAL DISPLAY PANEL - 473 ml Bottle Box

NDC 42546-175-16

SulfaCleanse® ^8/4
(sodium sulfacetamide 8% & sulfur 4%)

Topical Suspension in a vehicle
containing Green Tea and Aloe

Rx only
16 fl oz (473 ml)

PRUGEN®
PHARMACEUTICALS